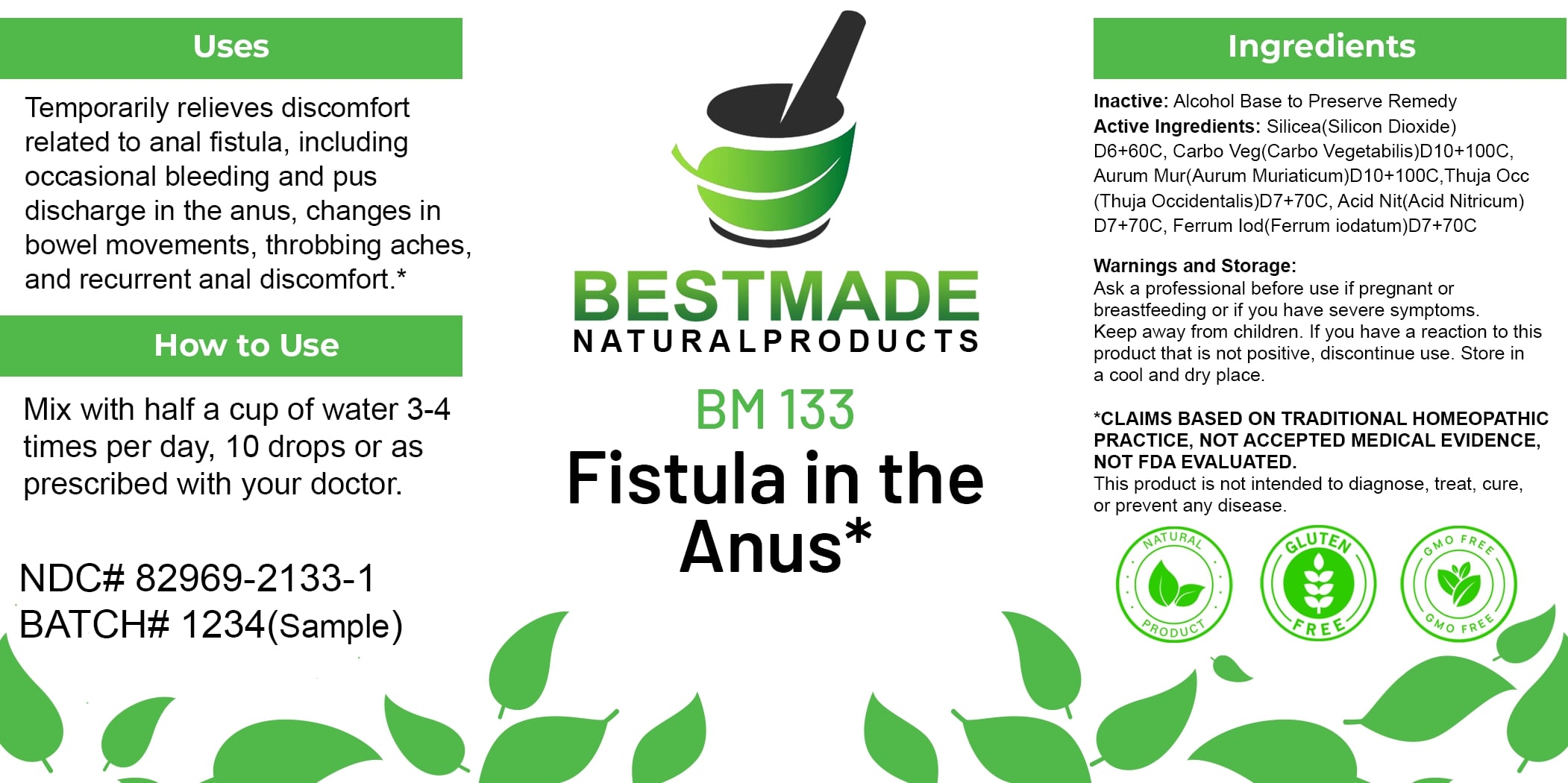 DRUG LABEL: Bestmade Natural Products BM133
NDC: 82969-2133 | Form: LIQUID
Manufacturer: Bestmade Natural Products
Category: homeopathic | Type: HUMAN OTC DRUG LABEL
Date: 20250212

ACTIVE INGREDIENTS: SILICA 30 [hp_C]/30 [hp_C]; FERROUS IODIDE 30 [hp_C]/30 [hp_C]; ACTIVATED CHARCOAL 30 [hp_C]/30 [hp_C]; THUJA OCCIDENTALIS LEAFY TWIG 30 [hp_C]/30 [hp_C]; GOLD TRICHLORIDE 30 [hp_C]/30 [hp_C]; NITRIC ACID 30 [hp_C]/30 [hp_C]
INACTIVE INGREDIENTS: ALCOHOL 30 [hp_C]/30 [hp_C]

BM133

DOSAGE AND ADMINISTRATION

How to Use

Mix with half a cup of water 3-4 times per day, 10 drops or as prescribed with your doctor.

INACTIVE INGREDIENT

Ingredients

Inactive: Alcohol Base to Preserve Remedy

Uses

Temporarily relieves discomfort related to anal fistula, including occasional bleeding and pus discharge in the anus, changes in bowel movements, throbbing aches, and recurrent anal discomfort.*

*CLAIMS BASED ON TRADITIONAL HOMEOPATHIC PRACTICE, NOT ACCEPTED MEDICAL EVIDENCE, NOT FDA EVALUATED.

This product is not intended to diagnose, treat, cure, or prevent any disease.

Uses

Temporarily relieves discomfort related to anal fistula, including occasional bleeding and pus discharge in the anus, changes in bowel movements, throbbing aches, and recurrent anal discomfort.*

*CLAIMS BASED ON TRADITIONAL HOMEOPATHIC PRACTICE, NOT ACCEPTED MEDICAL EVIDENCE, NOT FDA EVALUATED.

This product is not intended to diagnose, treat, cure, or prevent any disease.

KEEP OUT OF REACH OF CHILDREN

Warnings and Storage:

Ask a professional before use if pregnant or breastfeeding or if you have severe symptoms. Keep away from children. If you have a reaction to this product that is not positive, discontinue use. Store in a cool and dry place.

Warnings and Storage:

Ask a professional before use if pregnant or breastfeeding or if you have severe symptoms. Keep away from children. If you have a reaction to this product that is not positive, discontinue use. Store in a cool and dry place.

*CLAIMS BASED ON TRADITIONAL HOMEOPATHIC PRACTICE, NOT ACCEPTED MEDICAL EVIDENCE, NOT FDA EVALUATED.

This product is not intended to diagnose, treat, cure, or prevent any disease.

Entire package label